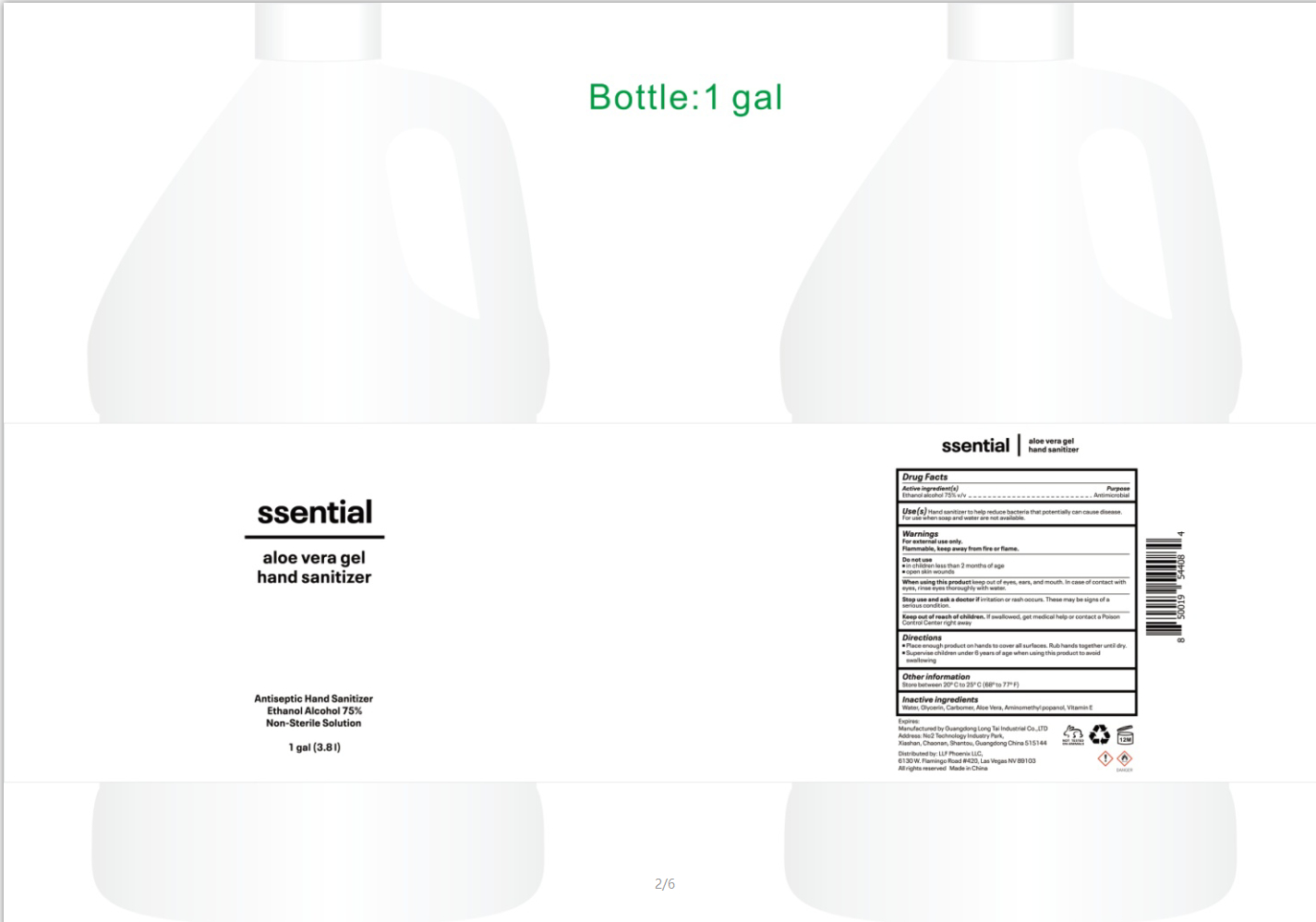 DRUG LABEL: ssential aloe vera gel hand sanitizer
NDC: 52807-020 | Form: LIQUID
Manufacturer: Guangdong Longtai Industry Co.,Ltd.
Category: otc | Type: HUMAN OTC DRUG LABEL
Date: 20200612

ACTIVE INGREDIENTS: ALCOHOL 2850 mL/3800 mL
INACTIVE INGREDIENTS: ALOE; WATER; GLYCERIN; CARBOMER HOMOPOLYMER, UNSPECIFIED TYPE; AMINOMETHYLPROPANOL; .ALPHA.-TOCOPHEROL

DOSAGE AND ADMINISTRATION

Store between 20° C to 25°C,(68° to77°F).

INACTIVE INGREDIENT

water, glycerin, carbomer, aminomethyl propanol, Aloe Vera, Vitamin E

INDICATIONS AND USAGE

■Place enough product on hands to cover all surfaces.
■Rub hands together until dry.

ACTIVE INGREDIENT

Ethanol Alcohol

keep out of reach of children

PURPOSE

Disinfection
Sterilization
No Rinseing

WARNINGS

For external use only. Flammable,keep away from fire or flame.Keep out of reach of children.If swallowed, get medical help or
contacta Poisn ControlCenter right away